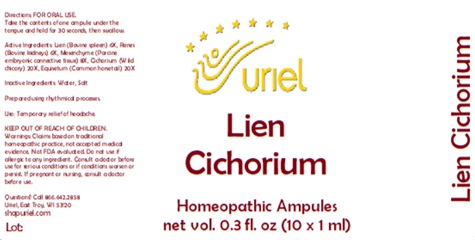 DRUG LABEL: Lien Cichorium
NDC: 48951-6033 | Form: LIQUID
Manufacturer: Uriel Pharmacy Inc.
Category: homeopathic | Type: HUMAN OTC DRUG LABEL
Date: 20250627

ACTIVE INGREDIENTS: BOS TAURUS SPLEEN 6 [hp_X]/1 mL; PORK KIDNEY 6 [hp_X]/1 mL; BOS TAURUS CARTILAGE 8 [hp_X]/1 mL; CICHORIUM INTYBUS WHOLE 20 [hp_X]/1 mL; EQUISETUM ARVENSE TOP 20 [hp_X]/1 mL
INACTIVE INGREDIENTS: WATER; SODIUM CHLORIDE

Lien Cichorium

INDICATIONS AND USAGE

Directions: FOR ORAL USE.

DOSAGE AND ADMINISTRATION

Take the contents of one ampule under the tongue and hold for 30 seconds, then swallow.

ACTIVE INGREDIENT

Active Ingredients: Lien (Bovine spleen) 6X, Renes (Bovine kidneys) 6X, Mesenchyme (Porcine embryonic connective tissue) 8X, Cichorium (Wild chicory) 20X, Equisetum (Common horsetail) 20X

Inactive Ingredients: Water, Salt

Prepared using rhythmical processes.

PURPOSE

Use: Temporary relief of headache.

KEEP OUT OF REACH OF CHILDREN.

WARNINGS

Warnings: Claims based on traditional homeopathic practice, not accepted medical evidence. Not FDA evaluated. Do not use if allergic to any ingredient. Consult a doctor before use for serious conditions or if conditions worsen or persist. If pregnant or nursing, consult a doctor before use.

QUESTIONS

Questions? Call 866.642.2858 Uriel, East Troy, WI 53120 shopuriel.com